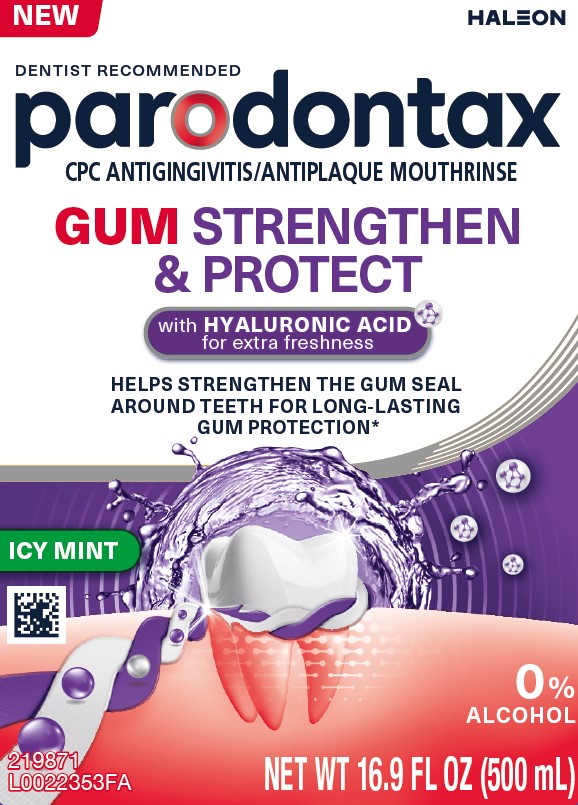 DRUG LABEL: Parodontax

NDC: 0135-0654 | Form: RINSE
Manufacturer: Haleon US Holdings LLC
Category: otc | Type: HUMAN OTC DRUG LABEL
Date: 20260105

ACTIVE INGREDIENTS: CETYLPYRIDINIUM CHLORIDE 0.7 mg/1 mL
INACTIVE INGREDIENTS: WATER; GLYCERIN; PROPYLENE GLYCOL; POLOXAMER 407; BENZOIC ACID; SACCHARIN SODIUM; SUCRALOSE; HYALURONATE SODIUM; BASIC BLUE 1

Drug Facts

Active ingredient

Cetylpyridinium chloride 0.07% w/w

Purposes

Antigingivitis, Antiplaque

Uses

helps prevent and reduce plaque that leads to

- gingivitis, an early form of gum disease
- bleeding gums

Warnings

Stop use and ask a dentist if

- irritation occurs
- gingivitis, bleeding, or redness persists for more than 2 weeks
- you have painful or swollen gums, pus from the gum line, loose teeth, or increasing space between the teeth. These may be signs or symptoms of periodontitis, a serious form of gum disease.

Keep out of reach of children under 6 years of age.

If more than used for rinsing is accidentally swallowed, get medical help or contact a Poison Control Center right away.

Directions

- adult and children 6 years of age and older:measure twice up to 10 milliliters mark inside of cap. Vigorously swish 20 milliliters of the rinse between your teeth twice a day for 30 seconds and then spit out. Do not swallow the rinse. Do not rinse with water. Do not drink from the bottle.
- children 6 years to under 12 years of age:supervise use
- children under 6 years of age:do not use

Other information

- this rinse is not intended to replace brushing or flossing
- may cause staining
- do not store above 25°C (77°F)
- this product may turn cloudy. Its antimicrobial properties are not affected.

Inactive ingredients

water, glycerin, propylene glycol, poloxamer 407, flavor, benzoic acid, sodium benzoate, sodium saccharin, sucralose, sodium hyaluronate, blue 1

Questions or comments?

1-866-844-2797

Additional Information

ALWAYS FOLLOW THE LABEL

Do not use if printed safety seal around cap is broken or missing.

*With continued twice daily use

Principal Display Panel

DENTIST RECOMMENDED

parodontax

CPC ANTIGINGIVITIS/ANTIPLAQUE MOUTHRINSE

GUM STRENGTHEN & PROTECT

with HYALURONIC ACIDfor extra freshness

HELPS STRENGTHEN THE GUM SEAL AROUND TEETH FOR LONG-LASTING GUM PROTECTION*

ICY MINT

0% ALCOHOL

NET WT 16.9 FL OZ (500 mL)